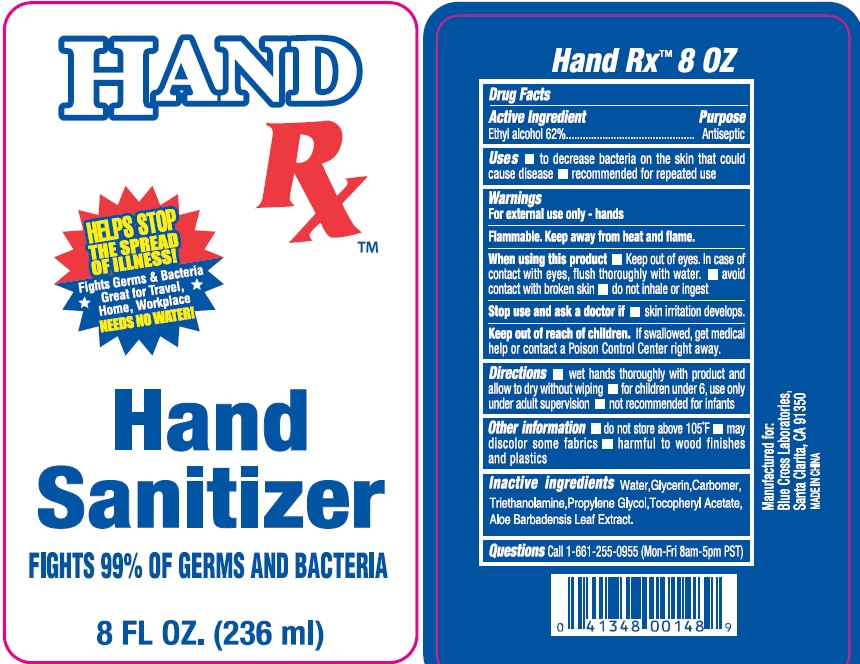 DRUG LABEL: Hand RX Hand Sanitizer
NDC: 74149-005 | Form: GEL
Manufacturer: Yiwu Yangjie Daily Chemicals Co.,Ltd.
Category: otc | Type: HUMAN OTC DRUG LABEL
Date: 20200511

ACTIVE INGREDIENTS: alcohol 62 mL/100 mL
INACTIVE INGREDIENTS: WATER; PROPYLENE GLYCOL; ALOE VERA LEAF; CARBOMER 934; GLYCERIN; .ALPHA.-TOCOPHEROL ACETATE; TROLAMINE

Drug facts

Active ingredient Purpose

Ethyl Alcohol 62% ... Antibacterial

PURPOSE

- decrease bacteria on the skin that could cause disease
- recommended for repeated use

KEEP OUT OF REACH OF CHILDREN

If swallowed, get medical help or contact a poison control center right away.

Directions:

- wet hands thoroughly with product and allow to dry without wiping
- for children under 6, use only under adult supervision
- not recommened for infants

WARNINGS

For external use only - hands
Flammable. Keep away from heat or flame.

When using this product

- Keep out of eyes. In case of contact with eye, flush thoroughly with water.
- avoid contact with broken skin
- do not inhale or ingest

Stop use and ask a doctor

- skin irritation develops.

DOSAGE AND ADMINISTRATION

wet hands thoroughly with product and allow to dry.

Other Information:

- do not store above 105℉
- may discolor some fabrics
- harmful to wood finished and plastics

INACTIVE INGREDIENT

Water, Glycerin, Carbomer, Triethanolamine, Propylene Glycol, Tocopheryl Acetate, Aloe Barbadensis Leaf Extract